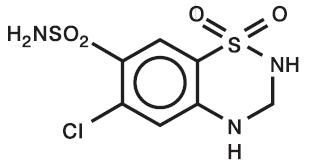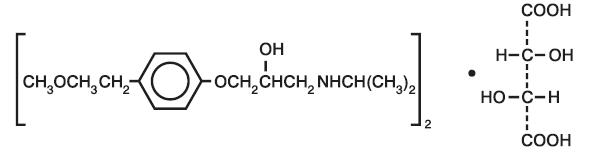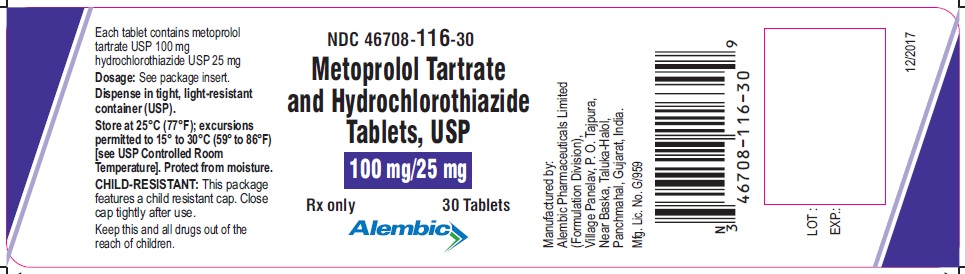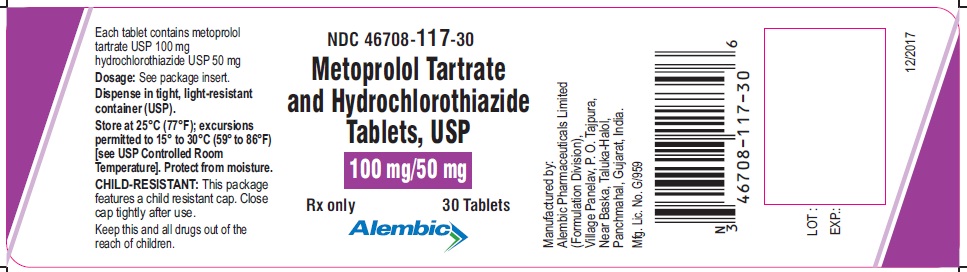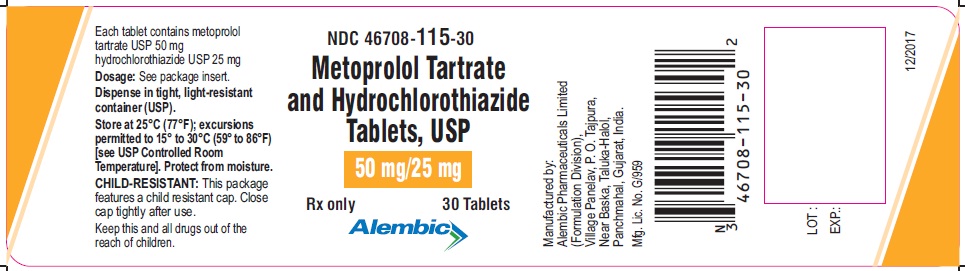 DRUG LABEL: Metoprolol Tartrate and Hydrochlorothiazide
NDC: 46708-115 | Form: TABLET
Manufacturer: Alembic Pharmaceuticals Limited
Category: prescription | Type: Human Prescription Drug Label
Date: 20230117

ACTIVE INGREDIENTS: METOPROLOL TARTRATE 50 mg/1 1; HYDROCHLOROTHIAZIDE 25 mg/1 1
INACTIVE INGREDIENTS: MICROCRYSTALLINE CELLULOSE; SODIUM STARCH GLYCOLATE TYPE A POTATO; SILICON DIOXIDE; POVIDONE, UNSPECIFIED; ANHYDROUS LACTOSE; STARCH, CORN; MAGNESIUM STEARATE

Metoprolol Tartrate and Hydrochlorothiazide Tablets USP
50 mg/25 mg, 100 mg/25 mg and 100 mg/50 mg
Beta Blocker/Diuretic Antihypertensive
Rx only
Prescribing Information

DESCRIPTION

Metoprolol tartrate and hydrochlorothiazide tablethas the antihypertensive effect of metoprolol tartrate, a selective beta1-adrenoreceptor blocking agent, and the antihypertensive and diuretic actions of hydrochlorothiazide. It is available as tablets for oral administration. The 50/25 tablets contain 50 mg of metoprolol tartrate USP and 25 mg of hydrochlorothiazide USP; the 100/25 tablets contain 100 mg of metoprolol tartrate USP and 25 mg of hydrochlorothiazide USP; and the 100/50 tablets contain 100 mg of metoprolol tartrate USP and 50 mg of hydrochlorothiazide USP. Metoprolol tartrate USP is (±)-1-(Isopropylamino)-3-[p-(2-methoxyethyl)phenoxy]-2-propanol L-(+)-tartrate (2:1) salt, and its structural formula is

Metoprolol tartrate USP is a white, crystalline powder. It is very soluble in water; freely soluble in methylene chloride, in chloroform, and in alcohol; slightly soluble in acetone; and insoluble in ether. Its molecular weight is 684.82.
Hydrochlorothiazide is 6-chloro-3,4-dihydro-2H-1,2,4-benzothiadiazine-7-sulfonamide 1,1- dioxide, and its structural formula is

Hydrochlorothiazide USP is a white, or practically white, practically odorless, crystalline powder. It is freely soluble in sodium hydroxide solution, in n-butylamine, and in dimethylformamide; sparingly soluble in methanol; slightly soluble in water; and insoluble in ether, in chloroform, and in dilute mineral acids. Its molecular weight is 297.73.
Inactive Ingredients: colloidal silicon dioxide, magnesium stearate, microcrystalline cellulose, sodium starch glycolate, povidone, lactose, pregelatinized starch.

CLINICAL PHARMACOLOGY

Metoprolol
Metoprolol is a beta-adrenergic receptor blocking agent. In vitro and in vivo animal studies have shown that it has a preferential effect on beta1 adrenoreceptors, chiefly located in cardiac muscle. This preferential effect is not absolute, however, and at higher doses, metoprolol also inhibits beta2 adrenoreceptors, chiefly located in the bronchial and vascular musculature.
Clinical pharmacology studies have confirmed the beta-blocking activity of metoprolol in man, as shown by (1) reduction in heart rate and cardiac output at rest and upon exercise, (2) reduction of systolic blood pressure upon exercise, (3) inhibition of isoproterenol-induced tachycardia, and (4) reduction of reflex orthostatic tachycardia.
Relative beta1 selectivity has been confirmed by the following: (1) In normal subjects, metoprolol is unable to reverse the beta2-mediated vasodilating effects of epinephrine. This contrasts with the effect of nonselective (beta1 plus beta2) beta blockers, which completely reverse the vasodilating effects of epinephrine. (2) In asthmatic patients, metoprolol reduces FEV1 and FVC significantly less than a nonselective beta blocker, propranolol at equivalent beta1-receptor blocking doses.
Metoprolol has no intrinsic sympathomimetic activity and only weak membrane-stabilizing activity. Metoprolol crosses the blood-brain barrier and has been reported in the CSF in a concentration 78% of the simultaneous plasma concentration. Animal and human experiments indicate that metoprolol slows the sinus rate and decreases AV nodal conduction.
In controlled clinical studies, metoprolol has been shown to be an effective antihypertensive agent when used alone or as concomitant therapy with thiazide-type diuretics, at dosages of 100 to 450 mg daily. In controlled, comparative, clinical studies, metoprolol has been shown to be as effective an antihypertensive agent as propranolol, methyldopa, and thiazide-type diuretics, and to be equally effective in supine and standing positions.
The mechanism of the antihypertensive effects of beta-blocking agents has not been elucidated. However, several possible mechanisms have been proposed: (1) competitive antagonism of catecholamines at peripheral (especially cardiac) adrenergic neuron sites, leading to decreased cardiac output; (2) a central effect leading to reduced sympathetic outflow to the periphery; and (3) suppression of renin activity.
Pharmacokinetics
In man, absorption of metoprolol is rapid and complete. Plasma levels following oral administration, however, approximate 50% of levels following intravenous administration, indicating about 50% first-pass metabolism.
Plasma levels achieved are highly variable after oral administration. Only a small fraction of the drug (about 12%) is bound to human serum albumin. Metoprolol is a racemic mixture of R- and S-enantiomers. Less than 5% of an oral dose of metoprolol is recovered unchanged in the urine; the rest is excreted by the kidneys as metabolites that appear to have no clinical significance. The systemic availability and half-life of metoprolol in patients with renal failure do not differ to a clinically significant degree from those in normal subjects. Consequently, no reduction in dosage is usually needed in patients with chronic renal failure.
In elderly subjects with clinically normal renal function, there are no significant differences in metoprolol pharmacokinetics compared to young subjects.
Metoprolol is extensively metabolized by the cytochrome P450 enzyme system in the liver. The oxidative metabolism of metoprolol is under genetic control with a major contribution of the polymorphic cytochrome P450 isoform 2D6 (CYP2D6). There are marked ethnic differences in the prevalence of the poor metabolizers (PM) phenotype. Approximately 7% of Caucasians and less than 1% Asian are poor metabolizers.
Poor CYP2D6 metabolizers exhibit several-fold higher plasma concentrations of metoprololthan extensive metabolizers with normal CYP2D6 activity. The elimination half-life of metoprolol is about 7.5 hours in poor metabolizers and 2.8 hours in extensive metabolizers. However, the CYP2D6 dependent metabolism of metoprololseems to have little or no effect on safety or tolerability of the drug. None of the metabolites of metoprololcontribute significantly to its beta-blocking effect.
Pharmacodynamics
Significant beta-blocking effect (as measured by reduction of exercise heart rate) occurs within 1 hour after oral administration, and its duration is dose-related. For example, a 50% reduction of the maximum registered effect after single oral doses of 20, 50, and 100 mg occurred at 3.3, 5, and 6.4 hours, respectively, in normal subjects. After repeated oral dosages of 100 mg twice daily, a significant reduction in exercise systolic blood pressure was evident at 12 hours.
There is a linear relationship between the log of plasma levels and reduction of exercise heart rate. However, antihypertensive activity does not appear to be related to plasma levels. Because of variable plasma levels attained with a given dose and lack of a consistent relationship of antihypertensive activity to dose, selection of proper dosage requires individual titration.
Hydrochlorothiazide
Thiazides affect the renal tubular mechanism of electrolyte reabsorption. At maximal therapeutic dosage, all thiazides are approximately equal in their diuretic potency. Thiazides increase excretion of sodium and chloride in approximately equivalent amounts. Natriuresis causes a secondary loss of potassium.
The mechanism of the antihypertensive effect of thiazides is unknown. Thiazides do not affect normal blood pressure.
Pharmacokinetics
Hydrochlorothiazide is rapidly absorbed, as indicated by peak plasma concentrations 1 to 2.5 hours after oral administration. Plasma levels of the drug are proportional to dose; the concentration in whole blood is 1.6 to 1.8 times higher than in plasma. Thiazides are eliminated rapidly by the kidney. After oral administration of 25- to 100-mg doses, 72 to 97% of the dose is excreted in the urine, indicating dose-independent absorption. Hydrochlorothiazide is eliminated from plasma in a biphasic fashion with a terminal half-life of 10 to 17 hours. Plasma protein binding is 67.9%. Plasma clearance is 15.9 to 30 L/hr; volume of distribution is 3.6 to 7.8 L/kg.
Gastrointestinal absorption of hydrochlorothiazide is enhanced when administered with food. Absorption is decreased in patients with congestive heart failure, and the pharmacokinetics are considerably different in these patients.
Pharmacodynamics
The onset of action of thiazides occurs in 2 hours and the peak effect at about 4 hours. The action persists for approximately 6 to 12 hours.

INDICATIONS AND USAGE

Metoprolol tartrate and hydrochlorothiazide tablets are indicated for the management of hypertension
This fixed-combination drug is not indicated for initial therapy of hypertension. If the fixed combination represents the dose titrated to the individual patient’s needs, therapy with the fixed combination may be more convenient than with the separate components.

CONTRAINDICATIONS

Metoprolol
Metoprolol tartrate tablets are contraindicated in sinus bradycardia, heart block greater than first degree, cardiogenic shock, and overt cardiac failure (see WARNINGS).
Hypersensitivity to metoprolol tartrate and related derivatives, or to any of the excipients; hypersensitivity to other beta blockers (cross sensitivity between beta blockers can occur).
Sick-sinus syndrome.
Severe peripheral arterial circulatory disorders.
Hydrochlorothiazide
Hydrochlorothiazide is contraindicated in patients with anuria or hypersensitivity to this or other sulfonamide-derived drugs (see WARNINGS).

WARNINGS

Metoprolol

Cardiac Failure: Sympathetic stimulation is a vital component supporting circulatory function in congestive heart failure, and beta blockade carries the potential hazard of further depressing myocardial contractility and precipitating more severe failure. In hypertensive patients who have congestive heart failure controlled by digitalis and diuretics, metoprolol should be administered cautiously.

In Patients Without a History of Cardiac Failure: Continued depression of the myocardium with beta-blocking agents over a period of time can, in some cases, lead to cardiac failure. At the first sign or symptom of impending cardiac failure, patients should be fully digitalized and/or given a diuretic. The response should be observed closely. If cardiac failure continues, despite adequate digitalization and diuretic therapy, metoprolol should be withdrawn.

Ischemic Heart Disease: Following abrupt cessation of therapy with certain beta-blocking agents, exacerbations of angina pectoris and in some cases, myocardial infarction have been reported. Even in the absence of overt angina pectoris, when discontinuing therapy, metoprolol should not be withdrawn abruptly, and patients should be cautioned against interruption of therapy without the physician’s advice (see PRECAUTIONS: Information for Patients).

Bronchospastic Diseases: PATIENTS WITH BRONCHOSPASTIC DISEASES SHOULD, IN GENERAL, NOT RECEIVE BETA BLOCKERS, including metoprolol tartrate and hydrochlorothiazide. Because of its relative beta1 selectivity, however, metoprolol may be used with caution in patients with bronchospastic disease who do not respond to, or cannot tolerate, other antihypertensive treatment. Since beta1 selectivity is not absolute, a beta2-stimulating agent should be administered concomitantly, and the lowest possible dose of metoprolol should be used. In these circumstances it would be prudent initially to administer metoprolol in smaller doses three times daily, instead of larger doses two times daily, to avoid the higher plasma levels associated with the longer dosing interval (see DOSAGE AND ADMINISTRATION).

Major Surgery: Chronically administered beta-blocking therapy should not be routinely withdrawn prior to major surgery; however, the impaired ability of the heart to respond to reflex adrenergic stimuli may augment the risks of general anesthesia and surgical procedures.

Diabetes and Hypoglycemia: Metoprolol should be used with caution in diabetic patients if a beta-blocking agent is required. Beta blockers, including metoprolol tartrate and hydrochlorothiazide, may mask tachycardia occurring with hypoglycemia, but other manifestations such as dizziness and sweating may not be significantly affected. Selective beta blockers do not potentiate insulin-induced hypoglycemia and, unlike nonselective beta blockers, do not delay recovery of blood glucose to normal levels.

Pheochromocytoma: If metoprolol tartrate is used in the setting of pheochromocytoma, it should be given in combination with an alpha blocker, and only after the alpha blocker has been initiated. Administration of beta blockers alone in the setting of pheochromocytoma has been associated with a paradoxical increase in blood pressure due to the attenuation of beta-mediated vasodilatation in skeletal muscle.

Thyrotoxicosis: Beta-adrenergic blockade may mask certain clinical signs (e.g., tachycardia) or hyperthyroidism. Patients suspected of developing thyrotoxicosis should be managed carefully to avoid abrupt withdrawal of beta blockade, which might precipitate a thyroid storm.

Hydrochlorothiazide

Thiazides should be used with caution in patients with severe renal disease. In patients with renal disease, thiazides may precipitate azotemia. Cumulative effects of the drug may develop in patients with impaired renal function.

Thiazides should be used with caution in patients with impaired hepatic function or progressive liver disease, since minor alterations of fluid and electrolyte imbalance may precipitate hepatic coma.

Thiazides may add to or potentiate the action of other antihypertensive drugs. Potentiation occurs with ganglionic or peripheral adrenergic blocking drugs.

Sensitivity reactions are more likely to occur in patients with a history of allergy or bronchial asthma.

The possibility of exacerbation or activation of systemic lupus erythematosus has been reported.

Acute Myopia and Secondary Angle-Closure Glaucoma: Hydrochlorothiazide, a sulfonamide, can cause an idiosyncratic reaction, resulting in acute transient myopia and acute angle-closure glaucoma. Symptoms include acute onset of decreased visual acuity or ocular pain and typically occur within hours to weeks of drug initiation. Untreated acute angle-closure glaucoma can lead to permanent vision loss. The primary treatment is to discontinue hydrochlorothiazide as rapidly as possible. Prompt medical or surgical treatments may need to be considered if the intraocular pressure remains uncontrolled. Risk factors for developing acute angle-closure glaucoma may include a history of sulfonamide or penicillin allergy.

PRECAUTIONS

General

Metoprolol: Metoprolol should be used with caution in patients with impaired hepatic function.
Hydrochlorothiazide: All patients receiving thiazide therapy should be observed for clinical signs of fluid or electrolyte imbalance, namely hyponatremia, hypochloremic alkalosis, and hypokalemia (see Laboratory Tests and Drug/Drug Interactions). Warning signs are dryness of mouth, thirst, weakness, lethargy, drowsiness, restlessness, muscle pains or cramps, muscular fatigue, hypotension, oliguria, tachycardia, and gastrointestinal disturbance, such as nausea or vomiting.
Hypokalemia may develop, especially in cases of brisk diuresis or severe cirrhosis.
Interference with adequate oral intake of electrolytes will also contribute to hypokalemia. Hypokalemia may be avoided or treated by the use of potassium supplements or foods with high potassium content.
Any chloride deficit is generally mild and usually does not require specific treatment, except under extraordinary circumstances (as in liver disease or renal disease). Dilutional hyponatremia may occur in edematous patients in hot weather; appropriate therapy is water restriction, rather than administration of salt, except in rare instances when the hyponatremia is life-threatening. In cases of actual salt depletion, appropriate replacement is the therapy of choice.
Hyperuricemia may occur or frank gout may be precipitated in certain patients receiving thiazide therapy.
Latent diabetes may become manifest during thiazide administration (see Drug/Drug Interactions).
The antihypertensive effects of the drug may be enhanced in the postsympathectomy patient.
If progressive renal impairment becomes evident, withholding or discontinuing diuretic therapy should be considered.
Calcium excretion is decreased by thiazides. Pathological changes in the parathyroid gland with hypercalcemia and hypophosphatemia have been observed in a few patients on prolonged thiazide therapy. The common complications of hyperparathyroidism, such as renal lithiasis, bone resorption, and peptic ulceration, have not been seen.
Thiazide diuretics have been shown to increase the urinary excretion of magnesium; this may result in hypomagnesemia.

Information for Patients

Patients should be advised to take metoprolol tartrate and hydrochlorothiazide tablets regularly and continuously, as directed, with or immediately following meals. If a dose should be missed, the patient should take only the next scheduled dose (without doubling it). Patients should not discontinue metoprolol tartrate and hydrochlorothiazide tablets without consulting the physician.
Patients should be advised (1) to avoid operating automobiles and machinery or engaging in other tasks requiring alertness until the patient’s response to therapy with metoprolol tartrate and hydrochlorothiazide has been determined; (2) to contact the physician if any difficulty in breathing occurs; (3) to inform the physician or dentist before any type of surgery that he or she is taking metoprolol tartrate and hydrochlorothiazide tablets.

Laboratory Tests

Metoprolol: Clinical laboratory findings may include elevated levels of serum transaminase, alkaline phosphatase, and lactate dehydrogenase.
Hydrochlorothiazide: Initial and periodic determinations of serum electrolytes to detect possible electrolyte imbalance should be performed at appropriate intervals.
Serum and urine electrolyte determinations are particularly important when the patient is vomiting excessively or receiving parenteral fluids.

Drug/Drug Interactions

Metoprolol: Catecholamine-depleting drugs (e.g., reserpine) may have an additive effect when given with beta-blocking agents. Patients treated with metoprolol plus a catecholamine depletor should therefore be closely observed for evidence of hypotension or marked bradycardia, which may produce vertigo, syncope, or postural hypotension.
Both digitalis glycosides and beta blockers slow atrioventricular conduction and decrease heart rate. Concomitant use can increase the risk of bradycardia.
Risk of Anaphylactic Reaction: While taking beta blockers, patients with a history of severe anaphylactic reaction to a variety of allergens may be more reactive to repeated challenge, either accidental, diagnostic, or therapeutic. Such patients may be unresponsive to the usual doses of epinephrine used to treat allergic reaction.
General Anesthetics
Some inhalation anesthetics may enhance the cardiodepressant effect of beta blockers (see WARNINGS; Metoprolol; Major Surgery).
CYP2D6 Inhibitors
Potent inhibitors of the CYP2D6 enzyme may increase the plasma concentration of metoprolol. Strong inhibition of CYP2D6 would mimic the pharmacokinetics of CYP2D6 poor metabolizer. Caution should therefore be exercised when administering potent CYP2D6 inhibitors with metoprolol. Known clinically significant potent inhibitors of CYP2D6 are antidepressants such as fluoxetine, paroxetine or bupropion, antipsychotics such as thioridazine, antiarrhythmics such as quinidine or propafenone, antiretrovirals such as ritonavir, antihistamines such as diphenhydramine, antimalarials such as hydroxychloroquine or quinidine, antifungals such as terbinafine and medications for stomach ulcers such as cimetidine.
Clonidine
If a patient is treated with clonidine and metoprolol concurrently, and clonidine treatment is to be discontinued, metoprolol should be stopped several days before clonidine is withdrawn. Rebound hypertension that can follow withdrawal of clonidine may be increased in patients receiving concurrent beta blocker treatment.
Hydrochlorothiazide: Hypokalemia can sensitize or exaggerate the response of the heart to the toxic effects of digitalis (e.g., increased ventricular irritability).
Hypokalemia may develop during concomitant use of steroids or ACTH.
Insulin requirements in diabetic patients may be increased, decreased, or unchanged.
Thiazides may decrease arterial responsiveness to norepinephrine, but not enough to preclude effectiveness of the pressor agent for therapeutic use.
Thiazides may increase the responsiveness to tubocurarine.
Lithium renal clearance is reduced by thiazides, increasing the risk of lithium toxicity.
There have been rare reports in the literature of hemolytic anemia occurring with the concomitant use of hydrochlorothiazide and methyldopa.
Concurrent administration of some nonsteroidal anti-inflammatory agents may reduce the diuretic, natriuretic and antihypertensive effects of thiazide diuretics.
Cholestyramine and colestipol resins: Absorption of hydrochlorothiazide is impaired in the presence of anionic exchange resins. Single doses of either cholestyramine or colestipol resins bind the hydrochlorothiazide and reduce its absorption from the gastrointestinal tract by up to 85% and 43%, respectively.

Drug/Laboratory Test Interactions

Hydrochlorothiazide: Thiazides may decrease serum levels of protein-bound iodine without signs of thyroid disturbance. Thiazides should be discontinued before tests for parathyroid function are made. (see General, Hydrochlorothiazide, Calcium excretion).

Carcinogenesis, Mutagenesis, Impairment of Fertility

Metoprolol Tartrate and Hydrochlorothiazide: Carcinogenicity and mutagenicity studies have not been conducted with metoprolol tartrate and hydrochlorothiazide tablets. Metoprolol tartrate and hydrochlorothiazide tablets produced no evidence of impaired fertility in male or female rats administered gavaged doses up to 200/50 mg/kg (100/50 times the maximum recommended daily human dose) prior to mating and throughout gestation and rearing of young.
Metoprolol: Long-term studies in animals have been conducted to evaluate carcinogenic potential. In a 2-year study in rats at three oral dosage levels of up to 800 mg/kg per day, there was no increase in the development of spontaneously occurring benign or malignant neoplasms of any type. The only histologic changes that appeared to be drug related were an increased incidence of generally mild focal accumulation of foamy macrophages in pulmonary alveoli and a slight increase in biliary hyperplasia. In a 21-month study in Swiss albino mice at three oral dosage levels of up to 750 mg/kg per day, benign lung tumors (small adenomas) occurred more frequently in female mice receiving the highest dose than in untreated control animals. There was no increase in malignant or total (benign plus malignant) lung tumors, or in the overall incidence of tumors or malignant tumors. This 21-month study was repeated in CD-1 mice, and no statistically or biologically significant differences were observed between treated and control mice of either sex for any type of tumor.
All mutagenicity tests performed (a dominant lethal study in mice, chromosome studies in somatic cells, a Salmonella/mammalian-microsome mutagenicity test, and a nucleus anomaly test in somatic interphase nuclei) were negative.
No evidence of impaired fertility due to metoprolol was observed in a study performed in rats at doses up to 55.5 times the maximum daily human dose of 450 mg.
Hydrochlorothiazide: Two-year feeding studies in mice and rats conducted under the auspices of the National Toxicology Program (NTP) uncovered no evidence of a carcinogenic potential of hydrochlorothiazide in female mice (at doses up to approximately 600 mg/kg/day) or in male and female rats (at doses up to approximately 100 mg/kg/day). The NTP, however, found equivocal evidence for hepatocarcinogenicity in male mice.
Hydrochlorothiazide was not genotoxic in in vitro assays using strains TA 98, TA 100, TA 1535, TA 1537, and TA 1538 of Salmonella typhimurium (Ames assay) and in the Chinese Hamster Ovary (CHO) test for chromosomal aberrations, or in in vivo assays using mouse germinal cell chromosomes, Chinese hamster bone marrow chromosomes, and the Drosophila sex-linked recessive lethal trait gene. Positive test results were obtained only in the in vitro CHO Sister Chromatid Exchange (clastogenicity) and in the Mouse Lymphoma Cell (mutagenicity) assays, using concentrations of hydrochlorothiazide from 43 to 1300 ⛤g/mL, and in the Aspergillus nidulans nondisjunction assay at an unspecified concentration.
Hydrochlorothiazide had no adverse effects on the fertility of mice and rats of either sex in studies wherein these species were exposed, via their diet, to doses of up to 100 and 4 mg/kg/day, respectively, prior to mating and throughout gestation.

Pregnancy: Teratogenic Effects. Pregnancy Category C

Metoprolol Tartrate and Hydrochlorothiazide: No evidence of adverse effects on pregnancy or the fetus were observed in rats when dams were administered gavaged doses up to 200/50 mg/kg of metoprolol tartrate and hydrochlorothiazide tablets (100/50 times the maximum recommended daily human dose) during the period of organogenesis. Increased postimplantation loss and decreased postnatal survival were observed with these doses when administered later in pregnancy (gestation days 15 to 21). In rabbits, increased fetal loss was observed with oral doses of 25/6.25 mg/kg of metoprolol tartrate and hydrochlorothiazide tablets (12/6 times the maximum recommended daily human dose), but not with lower doses. There are no adequate and well-controlled studies of metoprolol tartrate and hydrochlorothiazide tablets in pregnant women. Metoprolol tartrate and hydrochlorothiazide tablets should be used during pregnancy only if the potential benefit justifies the potential risk to the fetus.
Metoprolol: Metoprolol has been shown to increase postimplantation loss and decrease neonatal survival in rats at doses up to 55.5 times the maximum daily human dose of 450 mg. Distribution studies in mice confirm exposure of the fetus when metoprolol is administered to the pregnant animal. These studies have revealed no evidence of teratogenicity.
Hydrochlorothiazide: Studies in which hydrochlorothiazide was orally administered to pregnant mice and rats during their respective periods of major organogenesis at doses up to 3000 and 1000 mg/kg/day, respectively, provided no evidence of harm to the fetus.
Nonteratogenic Effects
Hydrochlorothiazide: Thiazides cross the placental barrier and appear in cord blood, and there is a risk of fetal or neonatal jaundice, thrombocytopenia, and possibly other adverse reactions that have occurred in adults.

Nursing Mothers

Metoprolol is excreted in breast milk in a very small quantity. An infant consuming 1 liter of breast milk daily would receive a dose of metoprolol of less than 1 mg. Thiazides are also excreted in breast milk. If the use of metoprolol tartrate and hydrochlorothiazide tablets is deemed essential, the patient should stop nursing.

Pediatric Use

Safety and effectiveness in pediatric patients have not been established.

Geriatric Use

Clinical studies of metoprolol tartrate and hydrochlorothiazide tablets did not include sufficient numbers of subjects aged 65 and over to determine whether they respond differently from younger subjects. Other reported clinical experience has not identified differences in responses between the elderly and younger patients. Hydrochlorothiazide is known to be substantially excreted by the kidney, and the risk of toxic reactions to this drug may be greater in patients with impaired renal function. Because elderly patients are more likely to have decreased renal function, care should be taken in dose selection, and it may be useful to monitor renal function (see WARNINGS). In general, dose selection for an elderly patient should be cautious, usually starting at the low end of the dosing range, reflecting the greater frequency of decreased hepatic, renal, or cardiac function, and concomitant disease or other drug therapy.

ADVERSE REACTIONS

Metoprolol Tartrate and Hydrochlorothiazide
The following adverse reactions were reported in controlled clinical studies of the combination of metoprolol tartrate and hydrochlorothiazide.
Body as a Whole: Fatigue or lethargy and flu syndrome have each been reported in about 10 in 100 patients.
Nervous System: Dizziness or vertigo, drowsiness or somnolence, and headache have each occurred in about 10 in 100 patients. Nightmare has occurred in 1 in 100 patients.
Cardiovascular: Bradycardia has occurred in about 6 in 100 patients. Decreased exercise tolerance and dyspnea have each occurred in about 1 of 100 patients.
Digestive: Diarrhea, digestive disorder, dry mouth, nausea or vomiting, and constipation have each occurred in about 1 in 100 patients.
Metabolic and Nutritional: Hypokalemia has occurred in fewer than 10 in 100 patients. Edema, gout, and anorexia have each occurred in 1 in 100 patients.
Special Senses: Blurred vision, tinnitus, and earache have each been reported in 1 in 100 patients.
Skin: Sweating and purpura have each occurred in 1 in 100 patients.
Urogenital: Impotence has occurred in 1 in 100 patients.
Musculoskeletal: Muscle pain has occurred in 1 in 100 patients.
Metoprolol
Most adverse effects have been mild and transient.
Central Nervous System: Tiredness and dizziness have occurred in about 10 of 100 patients. Depression has been reported in about 5 of 100 patients. Mental confusion and short-term memory loss have been reported. Headache, nightmares, and insomnia have also been reported, but a drug relationship is not clear.
Cardiovascular: Shortness of breath and bradycardia have occurred in approximately 3 of 100 patients. Cold extremities; arterial insufficiency, usually of the Raynaud type; palpitations; and congestive heart failure have been reported. Gangrene in patients with pre-existing severe peripheral circulatory disorders has also been reported very rarely (see CONTRAINDICATIONS, WARNINGS, and PRECAUTIONS).
Respiratory: Wheezing (bronchospasm) has been reported in fewer than 1 of 100 patients (see WARNINGS). Rhinitis has also been reported.
Gastrointestinal: Diarrhea has occurred in about 5 of 100 patients. Nausea, gastric pain, constipation, flatulence, and heartburn have been reported in 1 of 100, or fewer, patients. Vomiting was a common occurrence. Postmarketing experience reveals very rare reports of hepatitis, jaundice and non-specific hepatic dysfunction. Isolated cases of transaminase, alkaline phosphatase, and lactic dehydrogenase elevations have also been reported.
Hypersensitive Reactions: Pruritus has occurred in fewer than 1 of 100 patients. Rash has been reported. Very rarely, photosensitivity and worsening of psoriasis has been reported.
Miscellaneous: Peyronie’s disease has been reported in fewer than 1 of 100,000 patients. Alopecia has been reported. There have been very rare reports of weight gain, arthritis, and retroperitoneal fibrosis (relationship to metoprolol has not been definitely established).
The oculomucocutaneous syndrome associated with the beta blocker practolol has not been reported with metoprolol.
Potential Adverse Reactions
A variety of adverse reactions not listed above have been reported with other beta-adrenergic blocking agents and should be considered potential adverse reactions to metoprolol.
Central Nervous System: Reversible mental depression progressing to catatonia; visual disturbances; hallucinations; an acute reversible syndrome characterized by disorientation for time and place, short-term memory loss, emotional lability, slightly clouded sensorium, and decreased performance on neuropsychometrics.
Cardiovascular: Intensification of AV block (see CONTRAINDICATIONS).
Hematologic: Agranulocytosis, nonthrombocytopenic purpura, thrombocytopenic purpura.
Hypersensitive Reactions: Fever combined with aching and sore throat, laryngospasm, and respiratory distress.
Postmarketing Experience
The following adverse reactions have been reported during postapproval use of metoprolol: confusional state, an increase in blood triglycerides and a decrease in High Density Lipoprotein (HDL). Because these reports are from a population of uncertain size and are subject to confounding factors, it is not possible to reliably estimate their frequency.
Hydrochlorothiazide
The following adverse reactions have been observed, but there has not been enough systematic collection of data to support an estimate of their frequency. Consequently the reactions are categorized by organ systems and are listed in decreasing order of severity and not frequency.
Digestive: Pancreatitis, jaundice (intrahepatic cholestatic), sialadenitis, vomiting, diarrhea, cramping, nausea, gastric irritation, constipation, anorexia.
Cardiovascular: Orthostatic hypotension (may be potentiated by alcohol, barbiturates, or narcotics).
Neurologic: Vertigo, dizziness, transient blurred vision, headache, paresthesia, xanthopsia, weakness, restlessness.
Musculoskeletal: Muscle spasm.
Hematologic: Aplastic anemia, agranulocytosis, leukopenia, thrombocytopenia.
Metabolic: Hyperglycemia, glycosuria, hyperuricemia.
Hypersensitive Reactions: Necrotizing angiitis, Stevens-Johnson syndrome, respiratory distress including pneumonitis and pulmonary edema, purpura, urticaria, rash, photosensitivity.

OVERDOSAGE

Acute Toxicity
Several cases of overdosage with metoprolol have been reported, some leading to death. No deaths have been reported with hydrochlorothiazide.
Oral LD50’s (mg/kg): mice, 1158 (metoprolol); rats, 3090 (metoprolol), 2750 (hydrochlorothiazide).
Signs and Symptoms
Metoprolol: Potential signs and symptoms associated with overdosage with metoprolol are bradycardia, hypotension, bronchospasm, and cardiac failure.
Hydrochlorothiazide: The most prominent feature of poisoning is acute loss of fluid and electrolytes.
Cardiovascular: Tachycardia, hypotension, shock.
Neuromuscular: Weakness, confusion, dizziness, cramps of the calf muscles, paresthesia, fatigue, impairment of consciousness.
Digestive: Nausea, vomiting, thirst.
Renal: Polyuria, oliguria, or anuria (due to hemoconcentration).
Laboratory Findings: Hypokalemia, hyponatremia, hypochloremia, alkalosis; increased BUN (especially in patients with renal insufficiency).
Combined Poisoning: Signs and symptoms may be aggravated or modified by concomitant intake of antihypertensive medication, barbiturates, curare, digitalis (hypokalemia), corticosteroids, narcotics, or alcohol.
Treatment
There is no specific antidote.
On the basis of the pharmacologic actions of metoprolol tartrate and hydrochlorothiazide, the following general measures should be employed:
Elimination of the Drug: Inducement of vomiting, gastric lavage, and activated charcoal.
Bradycardia: Atropine should be administered. If there is no response to vagal blockade, isoproterenol should be administered cautiously.
Hypotension: The patient’s legs should be elevated and lost fluid and electrolytes (potassium, sodium) should be replaced. A vasopressor should be administered, e.g., levarterenol or dopamine.
Bronchospasm: A beta2-stimulating agent and/or a theophylline derivative should be administered.
Cardiac Failure: A digitalis glycoside and diuretic should be administered. In shock resulting from inadequate cardiac contractility, administration of dobutamine, isoproterenol, or glucagon may be considered.
Surveillance: Fluid and electrolyte balance (especially serum potassium) and renal function should be monitored until conditions become normal.

DOSAGE AND ADMINISTRATION

Dosage should be determined by individual titration (see INDICATIONS AND USAGE).
Hydrochlorothiazide is usually given at a dosage of 12.5 to 50 mg per day. The usual initial dosage of metoprolol tartrate tablets is 100 mg daily in single or divided doses. Dosage may be increased gradually until optimum blood pressure control is achieved. The effective dosage range is 100 to 450 mg per day. While once-daily dosing is effective and can maintain a reduction in blood pressure throughout the day, lower doses (especially 100 mg) may not maintain a full effect at the end of the 24-hour period, and larger or more frequent daily doses may be required. This can be evaluated by measuring blood pressure near the end of the dosing interval to determine whether satisfactory control is being maintained throughout the day. Beta1 selectivity diminishes as dosage of metoprolol tartrate tablets is increased.
The following dosage schedule may be used to administer from 100 to 200 mg of metoprolol tartrate per day and from 25 to 50 mg of hydrochlorothiazide per day:

Metoprolol Tartrate and Hydrochlorothiazide | Dosage
Tablets of 50/25 | 2 tablets per day in single or divided doses
Tablets of 100/25 | 1 to 2 tablets per day in single or divided doses
Tablets of 100/50 | 1 tablet per day in single or divided doses

Dosing regimens that exceed 50 mg of hydrochlorothiazide per day are not recommended. When necessary, another antihypertensive agent may be added gradually, beginning with 50% of the usual recommended starting dose to avoid an excessive fall in blood pressure.

HOW SUPPLIED

Metoprolol Tartrate and Hydrochlorothiazide Tablets USP are available containing 50 mg/25 mg, 100 mg/25 mg or 100 mg/50 mg of metoprolol
tartrate, USP and hydrochlorothiazide, USP.
50 mg/25 mg tablets are white to off-white colored, round shaped, biconvex, bevel edged scored uncoated tablet debossed with “L” on one
side of score line and “230” on another side of score line and plain on
other side.
NDC 46708-115-30 bottle of 30 tablets
NDC 46708-115-31 bottles of 100 tablets
NDC 46708-115-91 bottles of 1000 tablets
100 mg/25 mg tablets are white to off-white colored, oval shaped, biconvex, bevel edged scored uncoated tablet debossed with “L” on one
side of score line and “232” on another side of score line and plain on other side.
NDC 46708-116-30 bottle of 30 tablets
NDC 46708-116-31 bottle of 100 tablets
NDC 46708-116-71 bottle of 500 tablets
100 mg/50 mg tablets are white to off-white colored, capsule shaped, biconvex, bevel edged scored uncoated tablet debossed with “L” on one side
of score line and “231” on another side of score line and plain on other side.
NDC 46708-117-30 bottle of 30 tablets
NDC 46708-117-31 bottle of 100 tablets
NDC 46708-117-71 bottle of 500 tablets
Store at 25°C (77°F); excursions permitted to 15° to 30°C (59° to 86°F)
[see USP Controlled Room Temperature]. Protect from moisture.
Dispense in tight, light-resistant container (USP).
Call your doctor for medical advice about side effects. You may report side effects to FDA at 1-800-FDA-1088.
Manufactured by:
Alembic Pharmaceuticals Limited (Formulation Division),
Village Panelav, P. O. Tajpura, Near Baska,
Taluka-Halol, Panchmahal, Gujarat, India.
Issued: 02/2016

PACKAGE LABEL.PRINCIPAL DISPLAY PANEL 50 mg/25 mg

Metoprolol Tartrate and Hydrochlorothiazide Tablets USP 50 mg/25 mg (30 Tablets in 1 Bottle)
Each tablet contains metoprolol tartrate USP 50 mg hydrochlorothiazide USP 25 mg
46708-115-30

PACKAGE LABEL.PRINCIPAL DISPLAY PANEL 100 mg/25 mg

Metoprolol Tartrate and Hydrochlorothiazide Tablets USP 100 mg/25 mg (30 Tablets in 1 Bottle)
Each tablet contains metoprolol tartrate USP 100 mg hydrochlorothiazide USP 25 mg
46708-116-30

PACKAGE LABEL.PRINCIPAL DISPLAY PANEL 100 mg/50 mg

Metoprolol Tartrate and Hydrochlorothiazide Tablets USP 100 mg/50 mg (30 Tablets in 1 Bottle)
Each tablet contains metoprolol tartrate USP 100 mg hydrochlorothiazide USP 50 mg
46708-117-30